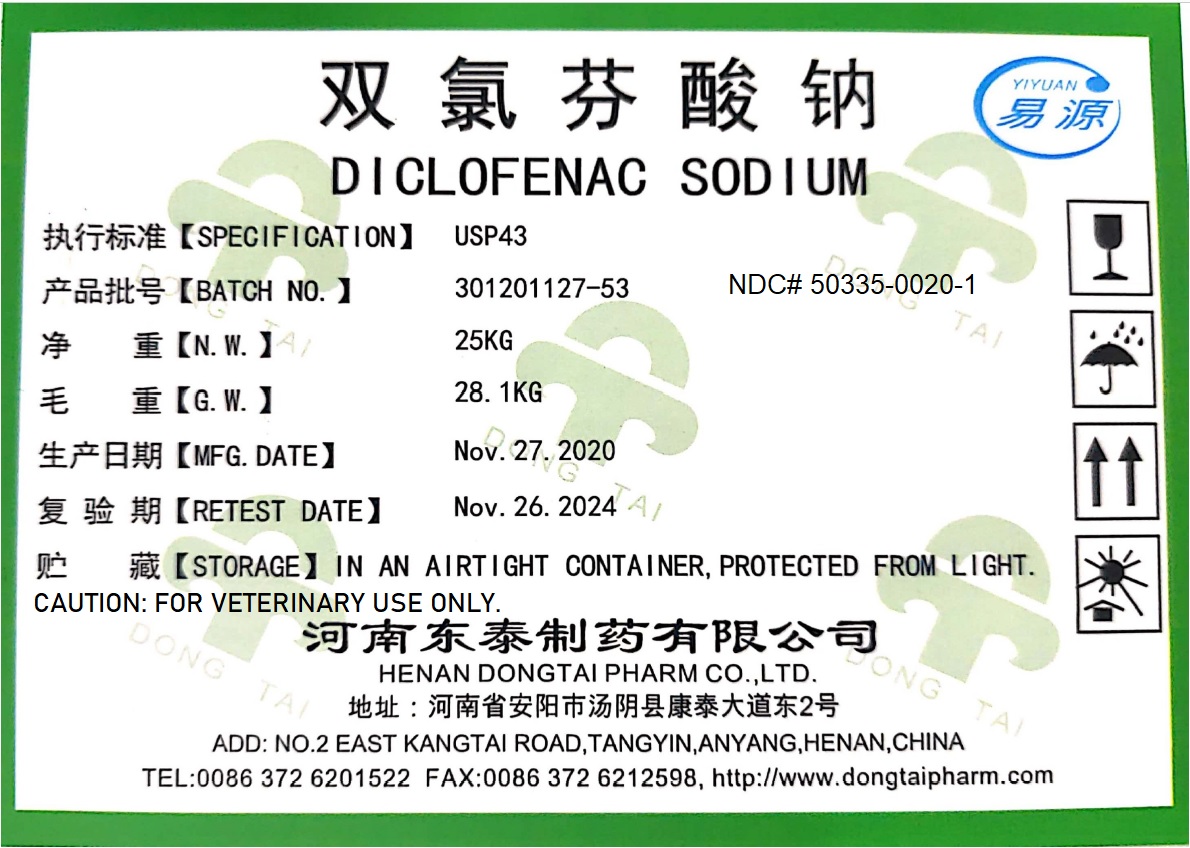 DRUG LABEL: Diclofenac Sodium
NDC: 50335-0020 | Form: POWDER
Manufacturer: Henan Dongtai Pharm Co., Ltd.
Category: other | Type: BULK INGREDIENT
Date: 20210208

ACTIVE INGREDIENTS: DICLOFENAC SODIUM 1 kg/1 kg

Diclofenac Sodium